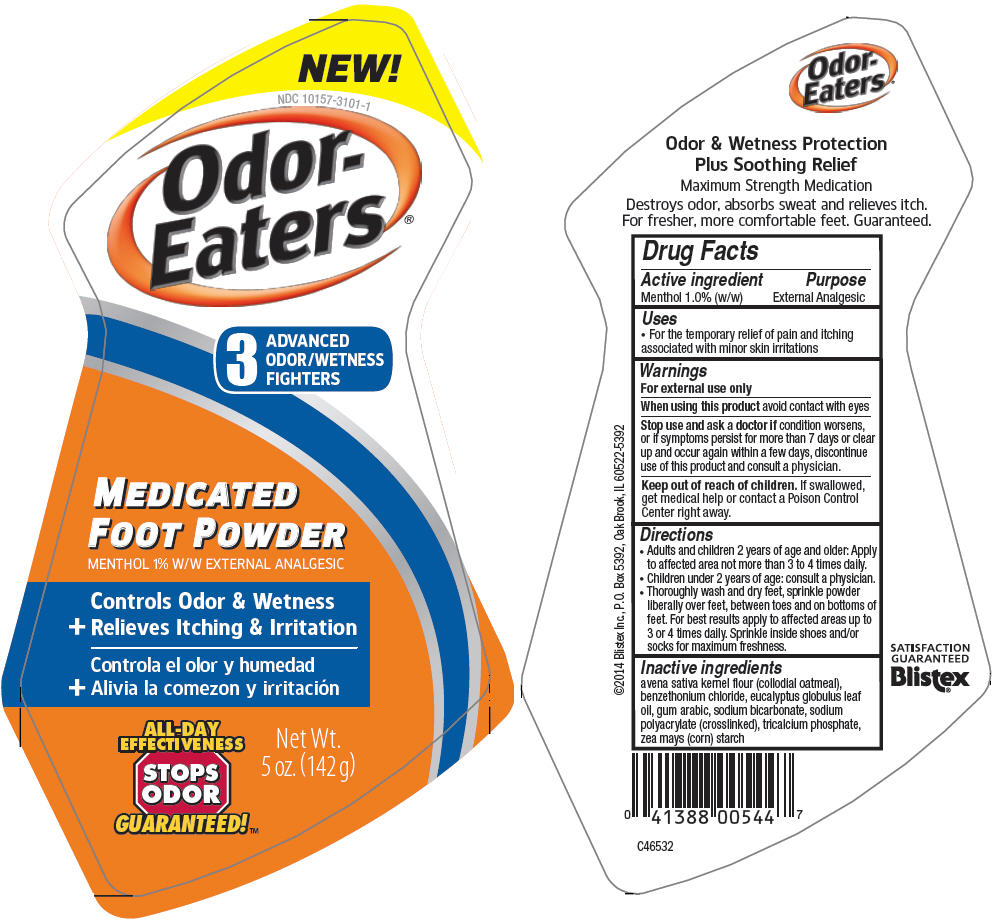 DRUG LABEL: Blistex Odor Eaters Medicated Foot
NDC: 10157-3101 | Form: POWDER
Manufacturer: Blistex Inc.
Category: otc | Type: HUMAN OTC DRUG LABEL
Date: 20150123

ACTIVE INGREDIENTS: MENTHOL, UNSPECIFIED FORM 1 g/100 g
INACTIVE INGREDIENTS: OATMEAL; BENZETHONIUM CHLORIDE; EUCALYPTUS OIL; ACACIA; SODIUM BICARBONATE; SODIUM POLYACRYLATE (8000 MW); TRICALCIUM PHOSPHATE; STARCH, CORN

Blistex Odor Eaters® Medicated Foot Powder

Drug Facts

Active ingredient

Menthol 1.0% (w/w)

Purpose

External Analgesic

Uses

- For the temporary relief of pain and itching associated with minor skin irritations

Warnings

For external use only

When using this product avoid contact with eyes

Stop use and ask a doctor if condition worsens, or if symptoms persist for more than 7 days or clear up and occur again within a few days, discontinue use of this product and consult a physician.

Keep out of reach of children. If swallowed, get medical help or contact a Poison Control Center right away.

Directions

- Adults and children 2 years of age and older: Apply to affected area not more than 3 to 4 times daily.
- Children under 2 years of age: consult a physician.
- Thoroughly wash and dry feet, sprinkle powder liberally over feet, between toes and on bottoms of feet. For best results apply to affected areas up to 3 or 4 times daily. Sprinkle inside shoes and/or socks for maximum freshness.

Inactive ingredients

avena sativa kernel flour (collodial oatmeal), benzethonium chloride, eucalyptus globulus leaf oil, gum arabic, sodium bicarbonate, sodium polyacrylate (crosslinked), tricalcium phosphate, zea mays (corn) starch

PRINCIPAL DISPLAY PANEL - 142 g Bottle Label

NEW!

NDC 10157-3101-1

Odor-
Eaters®

3
ADVANCED
ODOR/WETNESS
FIGHTERS

MEDICATED
FOOT POWDER

MENTHOL 1% W/W EXTERNAL ANALGESIC

Controls Odor & Wetness
+ Relieves Itching & Irritation

ALL-DAY
EFFECTIVENESS

STOPS
ODOR

GUARANTEED!™

Net Wt.
5 oz. (142 g)